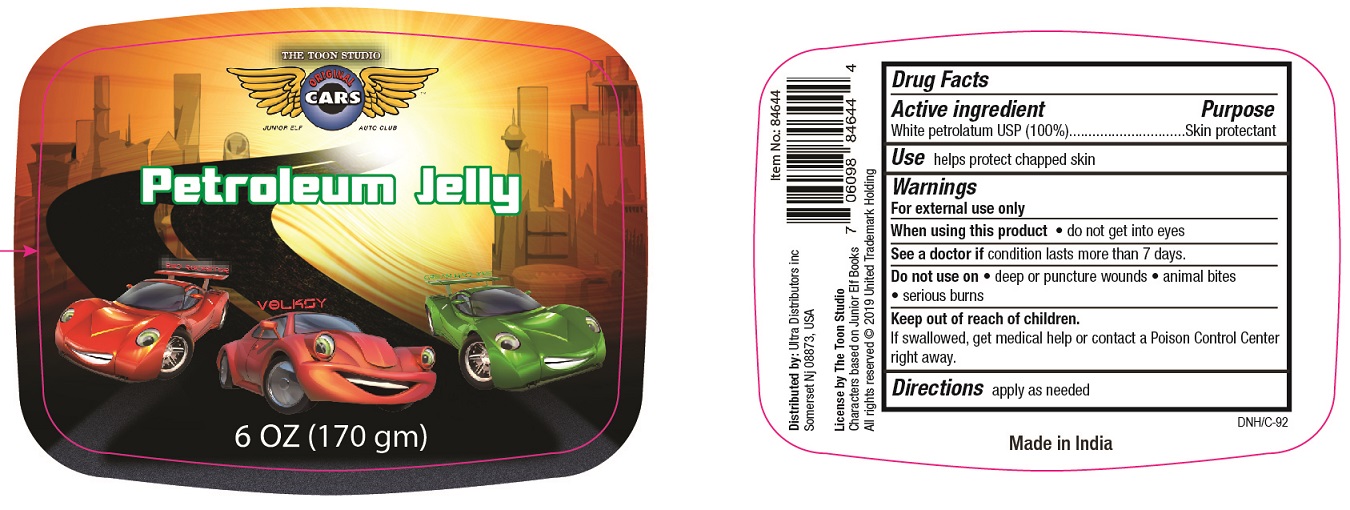 DRUG LABEL: Cars Petroleum
NDC: 78495-003 | Form: JELLY
Manufacturer: Ultra Distributors Inc.
Category: otc | Type: HUMAN OTC DRUG LABEL
Date: 20241219

ACTIVE INGREDIENTS: PETROLATUM 100 g/100 g

Cars Petroleum Jelly

Active Ingredient

White petrolatum USP (100%)

Purpose

Skin protectant

Uses

helps protect chapped skin

Warnings

For external use only

When using this product

- do not get into eyes

ASK DOCTOR

See a doctor ifcondition lasts more than 7 days.

Do not use on

- deep or puncture wounds
- animal bites
- serious burns

Keep out of reach of children

- If swallowed get medical help or contact a Poison Control Center right away.

Directions

apply as needed

Inactive ingredients

None

PACKAGE LABEL

PRINCIPAL DISPLAY PANEL

CARS PETROLEUM JELLY

NET WT 6 OZ (170 gm)